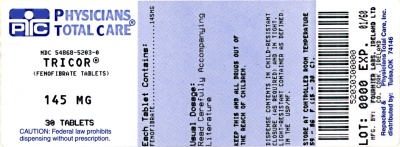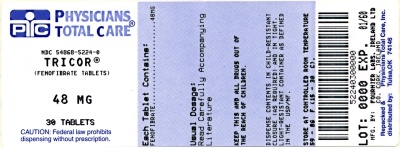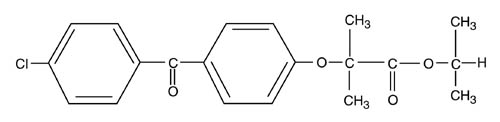 DRUG LABEL: Tricor
NDC: 54868-5224 | Form: TABLET
Manufacturer: Physicians Total Care, Inc.
Category: prescription | Type: HUMAN PRESCRIPTION DRUG LABEL
Date: 20091118

ACTIVE INGREDIENTS: FENOFIBRATE 48 mg/1 1
INACTIVE INGREDIENTS: POLYVINYL ALCOHOL; TITANIUM DIOXIDE; TALC; XANTHAN GUM; D&C YELLOW NO. 10; FD&C YELLOW NO. 6; FD&C BLUE NO. 2; HYPROMELLOSE; DOCUSATE SODIUM; SUCROSE; SODIUM LAURYL SULFATE; LACTOSE MONOHYDRATE; CELLULOSE, MICROCRYSTALLINE; CROSPOVIDONE; MAGNESIUM STEARATE

TRICOR®
48 mg and 145 mg
(fenofibrate tablets)

DESCRIPTION

TRICOR (fenofibrate tablets), is a lipid regulating agent available as tablets for oral administration. Each tablet contains 48 mg or 145 mg of fenofibrate. The chemical name for fenofibrate is 2-[4-(4-chlorobenzoyl) phenoxy]-2-methyl-propanoic acid, 1-methylethyl ester with the following structural formula:

The empirical formula is C20H21O4Cl and the molecular weight is 360.83; fenofibrate is insoluble in water. The melting point is 79-82°C. Fenofibrate is a white solid which is stable under ordinary conditions.

Inactive Ingredients

Each tablet contains hypromellose 2910 (3 cps), docusate sodium, sucrose, sodium lauryl sulfate, lactose monohydrate, silicified microcrystalline cellulose, crospovidone, and magnesium stearate.

In addition, individual tablets contain:

48 mg tablets

polyvinyl alcohol, titanium dioxide, talc, soybean lecithin, xanthan gum, D&C Yellow #10 aluminum lake, FD&C Yellow #6 /sunset yellow FCF aluminum lake, FD&C Blue #2 /indigo carmine aluminum lake.

145 mg tablets

polyvinyl alcohol, titanium dioxide, talc, soybean lecithin, xanthan gum.

CLINICAL PHARMACOLOGY

A variety of clinical studies have demonstrated that elevated levels of total cholesterol (total-C), low density lipoprotein cholesterol (LDL-C), and apolipoprotein B (apo B), an LDL membrane complex, are associated with human atherosclerosis. Similarly, decreased levels of high density lipoprotein cholesterol (HDL-C) and its transport complex, apolipoprotein A (apo AI and apo AII) are associated with the development of atherosclerosis. Epidemiologic investigations have established that cardiovascular morbidity and mortality vary directly with the level of total-C, LDL-C, and triglycerides, and inversely with the level of HDL-C. The independent effect of raising HDL-C or lowering triglycerides (TG) on the risk of cardiovascular morbidity and mortality has not been determined.

Fenofibric acid, the active metabolite of fenofibrate, produces reductions in total cholesterol, LDL cholesterol, apolipoprotein B, total triglycerides and triglyceride rich lipoprotein (VLDL) in treated patients. In addition, treatment with fenofibrate results in increases in high density lipoprotein (HDL) and apoproteins apoAI and apoAII.

The effects of fenofibric acid seen in clinical practice have been explained in vivo in transgenic mice and in vitro in human hepatocyte cultures by the activation of peroxisome proliferator activated receptor α (PPARα). Through this mechanism, fenofibrate increases lipolysis and elimination of triglyceride-rich particles from plasma by activating lipoprotein lipase and reducing production of apoprotein C-III (an inhibitor of lipoprotein lipase activity).

The resulting fall in triglycerides produces an alteration in the size and composition of LDL from small, dense particles (which are thought to be atherogenic due to their susceptibility to oxidation), to large buoyant particles. These larger particles have a greater affinity for cholesterol receptors and are catabolized rapidly. Activation of PPARα also induces an increase in the synthesis of apoproteins A-I, A-II and HDL-cholesterol.

Fenofibrate also reduces serum uric acid levels in hyperuricemic and normal individuals by increasing the urinary excretion of uric acid.

Pharmacokinetics/Metabolism

Plasma concentrations of fenofibric acid after administration of three 48 mg or one 145 mg tablets are equivalent under fed conditions to one 200 mg capsule.

Absorption

The absolute bioavailability of fenofibrate cannot be determined as the compound is virtually insoluble in aqueous media suitable for injection. However, fenofibrate is well absorbed from the gastrointestinal tract. Following oral administration in healthy volunteers, approximately 60% of a single dose of radiolabelled fenofibrate appeared in urine, primarily as fenofibric acid and its glucuronate conjugate, and 25% was excreted in the feces. Peak plasma levels of fenofibric acid occur within 6 to 8 hours after administration.

Exposure to fenofibric acid in plasma, as measured by Cmax and AUC, is not significantly different when a single 145 mg dose of fenofibrate is administered under fasting or nonfasting conditions.

Distribution

Upon multiple dosing of fenofibrate, fenofibric acid steady state is achieved within 9 days. Plasma concentrations of fenofibric acid at steady state are approximately double those following a single dose. Serum protein binding was approximately 99% in normal and hyperlipidemic subjects.

Metabolism

Following oral administration, fenofibrate is rapidly hydrolyzed by esterases to the active metabolite, fenofibric acid; no unchanged fenofibrate is detected in plasma.

Fenofibric acid is primarily conjugated with glucuronic acid and then excreted in urine. A small amount of fenofibric acid is reduced at the carbonyl moiety to a benzhydrol metabolite which is, in turn, conjugated with glucuronic acid and excreted in urine.

In vivo metabolism data indicate that neither fenofibrate nor fenofibric acid undergo oxidative metabolism (e.g., cytochrome P450) to a significant extent.

Excretion

After absorption, fenofibrate is mainly excreted in the urine in the form of metabolites, primarily fenofibric acid and fenofibric acid glucuronide. After administration of radiolabelled fenofibrate, approximately 60% of the dose appeared in the urine and 25% was excreted in the feces.

Fenofibric acid is eliminated with a half-life of 20 hours, allowing once daily administration in a clinical setting.

Special Populations

Geriatrics

In elderly volunteers 77 - 87 years of age, the oral clearance of fenofibric acid following a single oral dose of fenofibrate was 1.2 L/h, which compares to 1.1 L/h in young adults. This indicates that a similar dosage regimen can be used in the elderly, without increasing accumulation of the drug or metabolites.

Pediatrics

TRICOR has not been investigated in adequate and well-controlled trials in pediatric patients.

Gender

No pharmacokinetic difference between males and females has been observed for fenofibrate.

Race

The influence of race on the pharmacokinetics of fenofibrate has not been studied, however fenofibrate is not metabolized by enzymes known for exhibiting inter-ethnic variability. Therefore, inter-ethnic pharmacokinetic differences are very unlikely.

Renal Insufficiency

The pharmacokinetics of fenofibric acid was examined in patients with mild, moderate, and severe renal impairment. Patients with severe renal impairment (creatinine clearance [CrCl] ≤ 30 mL/min) showed 2.7-fold increase in exposure for fenofibric acid and increased accumulation of fenofibric acid during chronic dosing compared to that of healthy subjects. Patients with mild to moderate renal impairment (CrCl 30-80 mL/min) had similar exposure but an increase in the half-life for fenofibric acid compared to that of healthy subjects. Based on these findings, the use of TRICOR should be avoided in patients who have severe renal impairment and dose reduction is required in patients having mild to moderate renal impairment.

Hepatic Insufficiency

No pharmacokinetic studies have been conducted in patients having hepatic insufficiency.

Drug-drug Interactions

In vitro studies using human liver microsomes indicate that fenofibrate and fenofibric acid are not inhibitors of cytochrome (CYP) P450 isoforms CYP3A4, CYP2D6, CYP2E1, or CYP1A2. They are weak inhibitors of CYP2C8, CYP2C19 and CYP2A6, and mild-to-moderate inhibitors of CYP2C9 at therapeutic concentrations.

Potentiation of coumarin-type anticoagulants has been observed with prolongation of the prothrombin time/INR.

Bile acid sequestrants have been shown to bind other drugs given concurrently. Therefore, fenofibrate should be taken at least 1 hour before or 4-6 hours after a bile acid binding resin to avoid impeding its absorption. (See WARNINGS and PRECAUTIONS).

Concomitant administration of fenofibrate (equivalent to TRICOR 145 mg) with pravastatin (40 mg) once daily for 10 days has been shown to increase the mean Cmax and AUC values for pravastatin by 36% (range from 69% decrease to 321% increase) and 28% (range from 54% decrease to 128% increase), respectively, and for 3α-hydroxy-iso-pravastatin by 55% (range from 32% decrease to 314% increase) and 39% (range from 24% decrease to 261% increase), respectively in 23 healthy adults.

Concomitant administration of a single dose of fenofibrate (equivalent to 145 mg TRICOR) and a single dose of fluvastatin (40 mg) resulted in a small increase (approximately 15-16%) in exposure to (+)3R,5S-fluvastatin, the active enantiomer of fluvastatin.

A single dose of either pravastatin or fluvastatin had no clinically important effect on the pharmacokinetics of fenofibric acid.

Concomitant administration of fenofibrate (equivalent to TRICOR 145 mg) with atorvastatin (20 mg) once daily for 10 days resulted in approximately 17% decrease (range from 67% decrease to 44% increase) in atorvastatin AUC values in 22 healthy males. The atorvastatin Cmax values were not significantly affected by fenofibrate. The pharmacokinetics of fenofibric acid were not significantly affected by atorvastatin.

Concomitant administration of fenofibrate (equivalent to TRICOR 145 mg) once daily for 10 days with glimepiride (1 mg tablet) single dose simultaneously with the last dose of fenofibrate resulted in a 35% increase in mean AUC of glimepiride in healthy subjects. Glimepiride Cmax was not significantly affected by fenofibrate co-administration. There was no statistically significant effect of multiple doses of fenofibrate on glucose nadir or AUC with the baseline glucose concentration as the covariate after glimepiride administration in healthy volunteers. However, glucose concentrations at 24 hours remained statistically significantly lower after pretreatment with fenofibrate than with glimepiride alone. Glimepiride had no significant effect on the pharmacokinetics of fenofibric acid.

Concomitant administration of fenofibrate (54 mg) and metformin (850 mg) three times a day for 10 days resulted in no significant changes in the pharmacokinetics of fenofibric acid and metformin when compared with the two drugs administered alone in healthy subjects.

Concomitant administration of fenofibrate (equivalent to TRICOR 145 mg) once daily for 14 days with rosiglitazone tablet (rosiglitazone maleate) (8 mg) once daily for 5 days, Day 10 through Day 14, resulted in no significant changes in the pharmacokinetics of fenofibric acid and rosiglitazone when compared with the two drugs administered alone in healthy subjects.

Concomitant administration of fenofibrate (145 mg TRICOR) with ezetimibe (10 mg) once daily for 10 days to 18 healthy adults resulted in increases in total ezetimibe AUC, Cmax and Cmin of approximately 43%, 33% and 56%, respectively, and increases in ezetimibe glucuronide AUC, Cmax and Cmin of approximately 49%, 34% and 62%, respectively. The pharmacokinetics of fenofibric acid were not significantly affected by ezetimibe and the multiple-dose pharmacokinetics of free (unconjugated) ezetimibe were not significantly affected by fenofibrate.

Clinical Trials

Hypercholesterolemia (Heterozygous Familial and Nonfamilial) and Mixed Dyslipidemia (Fredrickson Types IIa and IIb)

The effects of fenofibrate at a dose equivalent to 145 mg TRICOR (fenofibrate tablets) per day were assessed from four randomized, placebo-controlled, double-blind, parallel-group studies including patients with the following mean baseline lipid values: total-C 306.9 mg/dL; LDL-C 213.8 mg/dL; HDL-C 52.3 mg/dL; and triglycerides 191.0 mg/dL. TRICOR therapy lowered LDL-C, Total-C, and the LDL-C/HDL-C ratio. TRICOR therapy also lowered triglycerides and raised HDL-C (see Table 1).

Table 1. Mean Percent Change in Lipid Parameters at End of Treatment†
Treatment Group | Total-C | LDL-C | HDL-C | TG
Pooled Cohort
Mean baseline lipid values (n=646) | 306.9 mg/dL | 213.8 mg/dL | 52.3 mg/dL | 191.0 mg/dL
All FEN (n=361) | -18.7%* | -20.6%* | +11.0%* | -28.9%*
Placebo (n=285) | -0.4% | -2.2% | +0.7% | +7.7%
Baseline LDL-C > 160 mg/dL and TG < 150 mg/dL (Type IIa)
Mean baseline lipid values (n=334) | 307.7 mg/dL | 227.7 mg/dL | 58.1 mg/dL | 101.7 mg/dL
All FEN (n=193) | -22.4%* | -31.4%* | +9.8%* | -23.5%*
Placebo (n=141) | +0.2% | -2.2% | +2.6% | +11.7%
Baseline LDL-C >160 mg/dL and TG ≥ 150 mg/dL (Type IIb)
Mean baseline lipid values (n=242) | 312.8 mg/dL | 219.8 mg/dL | 46.7 mg/dL | 231.9 mg/dL
All FEN (n=126) | -16.8%* | -20.1%* | +14.6%* | -35.9%*
Placebo (n=116) | -3.0% | -6.6% | +2.3% | +0.9%
† Duration of study treatment was 3 to 6 months.
* p = < 0.05 vs. Placebo

In a subset of the subjects, measurements of apo B were conducted. TRICOR treatment significantly reduced apo B from baseline to endpoint as compared with placebo (-25.1% vs. 2.4%, p < 0.0001, n=213 and 143 respectively).

Hypertriglyceridemia (Fredrickson Type IV and V)

The effects of fenofibrate on serum triglycerides were studied in two randomized, double-blind, placebo-controlled clinical trials^1 of 147 hypertriglyceridemic patients (Fredrickson Types IV and V). Patients were treated for eight weeks under protocols that differed only in that one entered patients with baseline triglyceride (TG) levels of 500 to 1500 mg/dL, and the other TG levels of 350 to 500 mg/dL. In patients with hypertriglyceridemia and normal cholesterolemia with or without hyperchylomicronemia (Type IV/V hyperlipidemia), treatment with fenofibrate at dosages equivalent to TRICOR 145 mg per day decreased primarily very low density lipoprotein (VLDL) triglycerides and VLDL cholesterol. Treatment of patients with Type IV hyperlipoproteinemia and elevated triglycerides often results in an increase of low density lipoprotein (LDL) cholesterol (see Table 2).

Table 2. Effects of TRICOR in Patients With Fredrickson Type IV/V Hyperlipidemia
Study 1 | Placebo |  |  |  | TRICOR
Baseline TG levels 350 to 499 mg/dL | N | Baseline (Mean) | Endpoint (Mean) | % Change (Mean) | N | Baseline (Mean) | Endpoint (Mean) | % Change (Mean)
Triglycerides | 28 | 449 | 450 | -0.5 | 27 | 432 | 223 | -46.2*
VLDL Triglycerides | 19 | 367 | 350 | 2.7 | 19 | 350 | 178 | -44.1*
Total Cholesterol | 28 | 255 | 261 | 2.8 | 27 | 252 | 227 | -9.1*
HDL Cholesterol | 28 | 35 | 36 | 4 | 27 | 34 | 40 | 19.6*
LDL Cholesterol | 28 | 120 | 129 | 12 | 27 | 128 | 137 | 14.5
VLDL Cholesterol | 27 | 99 | 99 | 5.8 | 27 | 92 | 46 | -44.7*
Study 2 | Placebo |  |  |  | TRICOR
Baseline TG levels 500 to 1500 mg/dL | N | Baseline (Mean) | Endpoint (Mean) | % Change (Mean) | N | Baseline (Mean) | Endpoint (Mean) | % Change (Mean)
Triglycerides | 44 | 710 | 750 | 7.2 | 48 | 726 | 308 | -54.5*
VLDL Triglycerides | 29 | 537 | 571 | 18.7 | 33 | 543 | 205 | -50.6*
Total Cholesterol | 44 | 272 | 271 | 0.4 | 48 | 261 | 223 | -13.8*
HDL Cholesterol | 44 | 27 | 28 | 5.0 | 48 | 30 | 36 | 22.9*
LDL Cholesterol | 42 | 100 | 90 | -4.2 | 45 | 103 | 131 | 45.0*
VLDL Cholesterol | 42 | 137 | 142 | 11.0 | 45 | 126 | 54 | -49.4*
* =p < 0.05 vs. Placebo

The effect of TRICOR on cardiovascular morbidity and mortality has not been determined.

INDICATIONS AND USAGE

Treatment of Hypercholesterolemia

TRICOR is indicated as adjunctive therapy to diet to reduce elevated LDL-C, Total-C, Triglycerides and Apo B, and to increase HDL-C in adult patients with primary hypercholesterolemia or mixed dyslipidemia (Fredrickson Types IIa and IIb). Lipid-altering agents should be used in addition to a diet restricted in saturated fat and cholesterol when response to diet and non-pharmacological interventions alone has been inadequate (see National Cholesterol Education Program [NCEP] Treatment Guidelines, below).

Treatment of Hypertriglyceridemia

TRICOR is also indicated as adjunctive therapy to diet for treatment of adult patients with hypertriglyceridemia (Fredrickson Types IV and V hyperlipidemia). Improving glycemic control in diabetic patients showing fasting chylomicronemia will usually reduce fasting triglycerides and eliminate chylomicronemia thereby obviating the need for pharmacologic intervention.

Markedly elevated levels of serum triglycerides (e.g. > 2,000 mg/dL) may increase the risk of developing pancreatitis. The effect of TRICOR therapy on reducing this risk has not been adequately studied.

Drug therapy is not indicated for patients with Type I hyperlipoproteinemia, who have elevations of chylomicrons and plasma triglycerides, but who have normal levels of very low density lipoprotein (VLDL). Inspection of plasma refrigerated for 14 hours is helpful in distinguishing Types I, IV and V hyperlipoproteinemia^2.

The initial treatment for dyslipidemia is dietary therapy specific for the type of lipoprotein abnormality. Excess body weight and excess alcoholic intake may be important factors in hypertriglyceridemia and should be addressed prior to any drug therapy. Physical exercise can be an important ancillary measure. Diseases contributory to hyperlipidemia, such as hypothyroidism or diabetes mellitus should be looked for and adequately treated. Estrogen therapy, thiazide diuretics and beta-blockers, are sometimes associated with massive rises in plasma triglycerides, especially in subjects with familial hypertriglyceridemia. In such cases, discontinuation of the specific etiologic agent may obviate the need for specific drug therapy of hypertriglyceridemia.

The use of drugs should be considered only when reasonable attempts have been made to obtain satisfactory results with non-drug methods. If the decision is made to use drugs, the patient should be instructed that this does not reduce the importance of adhering to diet. (See WARNINGS and PRECAUTIONS).

Fredrickson Classification of Hyperlipoproteinemias
 |  | Lipid Elevation
Type | Lipoprotein Elevated | Major | Minor
I (rare) | chylomicrons | TG | ↑↔C
IIa | LDL | C | -
IIb | LDL, VLDL | C | TG
III (rare) | IDL | C, TG | -
IV | VLDL | TG | ↑↔C
V (rare) | chylomicrons, VLDL | TG | ↑↔ C
C = cholesterol
TG = triglycerides
LDL= low density lipoprotein
VLDL= very low density lipoprotein
IDL = intermediate density lipoprotein

NCEP Treatment Guidelines: LDL-C Goals and Cutpoints for Therapeutic Lifestyle Changes and Drug Therapy in Different Risk Categories
Risk Category | LDL Goal (mg/dL) | LDL Level at Which to Initiate Therapeutic Lifestyle Changes (mg/dL) | LDL Level at Which to Consider Drug Therapy (mg/dL)
CHD† or CHD risk equivalents (10-year risk > 20%) | < 100 | ≥ 100 | ≥ 130 (100-129: drug optional)††
2+ Risk Factors (10-year risk ≤ 20%) | < 130 | ≥ 130 | 10-year risk 10%-20%: ≥ 130 10-year risk < 10%: ≥ 160
0-1 Risk Factor††† | < 160 | ≥ 160 | ≥ 190 (160-189: LDL-lowering drug optional)
† CHD = coronary heart disease
†† Some authorities recommend use of LDL-lowering drugs in this category if an LDL-C level of < 100 mg/dL cannot be achieved by therapeutic lifestyle changes. Others prefer use of drugs that primarily modify triglycerides and HDL-C, e.g., nicotinic acid or fibrate. Clinical judgement also may call for deferring drug therapy in this subcategory.
††† Almost all people with 0-1 risk factor have 10-year risk < 10%; thus, 10-year risk assessment in people with 0-1 risk factor is not necessary.

After the LDL-C goal has been achieved, if the TG is still ≥ 200 mg/dL, non HDL-C (total-C minus HDL-C) becomes a secondary target of therapy. Non-HDL-C goals are set 30 mg/dL higher than LDL-C goals for each risk category.

CONTRAINDICATIONS

TRICOR is contraindicated in patients who exhibit hypersensitivity to fenofibrate.

TRICOR is contraindicated in patients with hepatic or severe renal dysfunction, including primary biliary cirrhosis, and patients with unexplained persistent liver function abnormality.

TRICOR is contraindicated in patients with preexisting gallbladder disease (see WARNINGS).

WARNINGS

Liver Function

Fenofibrate at doses equivalent to 96 mg to 145 mg TRICOR per day has been associated with increases in serum transaminases [AST (SGOT) or ALT (SGPT)]. In a pooled analysis of 10 placebo-controlled trials, increases to > 3 times the upper limit of normal occurred in 5.3% of patients taking fenofibrate versus 1.1% of patients treated with placebo.

When transaminase determinations were followed either after discontinuation of treatment or during continued treatment, a return to normal limits was usually observed. The incidence of increases in transaminases related to fenofibrate therapy appear to be dose related. In an 8-week dose-ranging study, the incidence of ALT or AST elevations to at least three times the upper limit of normal was 13% in patients receiving dosages equivalent to 96 mg to 145 mg TRICOR per day and was 0% in those receiving dosages equivalent to 48 mg or less TRICOR per day, or placebo. Hepatocellular, chronic active and cholestatic hepatitis associated with fenofibrate therapy have been reported after exposures of weeks to several years. In extremely rare cases, cirrhosis has been reported in association with chronic active hepatitis.

Regular periodic monitoring of liver function, including serum ALT (SGPT) should be performed for the duration of therapy with TRICOR, and therapy discontinued if enzyme levels persist above three times the normal limit.

Cholelithiasis

Fenofibrate, like clofibrate and gemfibrozil, may increase cholesterol excretion into the bile, leading to cholelithiasis. If cholelithiasis is suspected, gallbladder studies are indicated. TRICOR therapy should be discontinued if gallstones are found.

Concomitant Oral Anticoagulants

Caution should be exercised when anticoagulants are given in conjunction with TRICOR because of the potentiation of coumarin-type anticoagulants in prolonging the prothrombin time/INR. The dosage of the anticoagulant should be reduced to maintain the prothrombin time/INR at the desired level to prevent bleeding complications. Frequent prothrombin time/INR determinations are advisable until it has been definitely determined that the prothrombin time/INR has stabilized.

Concomitant HMG-CoA Reductase Inhibitors

The combined use of TRICOR and HMG-CoA reductase inhibitors should be avoided unless the benefit of further alterations in lipid levels is likely to outweigh the increased risk of this drug combination.

Concomitant administration of fenofibrate (equivalent to TRICOR 145 mg) and pravastatin (40 mg) once daily for 10 days increased the mean Cmax and AUC values for pravastatin by 36% (range from 69% decrease to 321% increase) and 28% (range from 54% decrease to 128% increase), respectively, and for 3α-hydroxy-iso-pravastatin by 55% (range from 32% decrease to 314% increase) and 39% (range from 24% decrease to 261% increase), respectively. (See also CLINICAL PHARMACOLOGY, Drug-drug Interactions).

The combined use of fibric acid derivatives and HMG-CoA reductase inhibitors has been associated, in the absence of a marked pharmacokinetic interaction, in numerous case reports, with rhabdomyolysis, markedly elevated creatine kinase (CK) levels and myoglobinuria, leading in a high proportion of cases to acute renal failure.

The use of fibrates alone, including TRICOR, may occasionally be associated with myositis, myopathy, or rhabdomyolysis. Patients receiving TRICOR and complaining of muscle pain, tenderness, or weakness should have prompt medical evaluation for myopathy, including serum creatine kinase level determination. If myopathy/myositis is suspected or diagnosed, TRICOR therapy should be stopped.

Mortality

The effect of TRICOR on coronary heart disease morbidity and mortality and non-cardiovascular mortality has not been established.

Other Considerations

The Fenofibrate Intervention and Event Lowering in Diabetes (FIELD) study was a 5-year randomized, placebo-controlled study of 9795 patients with type 2 diabetes mellitus treated with fenofibrate. Fenofibrate demonstrated a non-significant 11% relative reduction in the primary outcome of coronary heart disease events (hazard ratio [HR] 0.89, 95% CI 0.75-1.05, p=0.16) and a significant 11% reduction in the secondary outcome of total cardiovascular disease events (HR 0.89 [0.80-0.99], p=0.04). There was a non-significant 11% (HR 1.11 [0.95, 1.29], p=0.18) and 19% (HR 1.19 [0.90, 1.57], p=0.22) increase in total and coronary heart disease mortality, respectively, with fenofibrate as compared to placebo.

In the Coronary Drug Project, a large study of post myocardial infarction of patients treated for 5 years with clofibrate, there was no difference in mortality seen between the clofibrate group and the placebo group. There was however, a difference in the rate of cholelithiasis and cholecystitis requiring surgery between the two groups (3.0% vs. 1.8%).

Because of chemical, pharmacological, and clinical similarities between TRICOR (fenofibrate tablets), Atromid-S (clofibrate), and Lopid (gemfibrozil), the adverse findings in 4 large randomized, placebo-controlled clinical studies with these other fibrate drugs may also apply to TRICOR.

In a study conducted by the World Health Organization (WHO), 5000 subjects without known coronary artery disease were treated with placebo or clofibrate for 5 years and followed for an additional one year. There was a statistically significant, higher age − adjusted all-cause mortality in the clofibrate group compared with the placebo group (5.70% vs. 3.96%, p = < 0.01). Excess mortality was due to a 33% increase in non-cardiovascular causes, including malignancy, post-cholecystectomy complications, and pancreatitis. This appeared to confirm the higher risk of gallbladder disease seen in clofibrate-treated patients studied in the Coronary Drug Project.

The Helsinki Heart Study was a large (n=4081) study of middle-aged men without a history of coronary artery disease. Subjects received either placebo or gemfibrozil for 5 years, with a 3.5 year open extension afterward. Total mortality was numerically higher in the gemfibrozil randomization group but did not achieve statistical significance (p = 0.19, 95% confidence interval for relative risk G:P = .91-1.64). Although cancer deaths trended higher in the gemfibrozil group (p = 0.11), cancers (excluding basal cell carcinoma) were diagnosed with equal frequency in both study groups. Due to the limited size of the study, the relative risk of death from any cause was not shown to be different than that seen in the 9 year follow-up data from World Health Organization study (RR=1.29). Similarly, the numerical excess of gallbladder surgeries in the gemfibrozil group did not differ statistically from that observed in the WHO study.

A secondary prevention component of the Helsinki Heart Study enrolled middle-aged men excluded from the primary prevention study because of known or suspected coronary heart disease. Subjects received gemfibrozil or placebo for 5 years. Although cardiac deaths trended higher in the gemfibrozil group, this was not statistically significant (hazard ratio 2.2, 95% confidence interval: 0.94-5.05). The rate of gallbladder surgery was not statistically significant between study groups, but did trend higher in the gemfibrozil group, (1.9% vs. 0.3%, p = 0.07). There was a statistically significant difference in the number of appendectomies in the gemfibrozil group (6/311 vs. 0/317, p = 0.029).

PRECAUTIONS

Initial Therapy

Laboratory studies should be done to ascertain that the lipid levels are consistently abnormal before instituting TRICOR therapy. Every attempt should be made to control serum lipids with appropriate diet, exercise, weight loss in obese patients, and control of any medical problems such as diabetes mellitus and hypothyroidism that are contributing to the lipid abnormalities. Medications known to exacerbate hypertriglyceridemia (beta blockers, thiazides, estrogens) should be discontinued or changed if possible prior to consideration of triglyceride-lowering drug therapy.

Continued Therapy

Periodic determination of serum lipids should be obtained during initial therapy in order to establish the lowest effective dose of TRICOR. Therapy should be withdrawn in patients who do not have an adequate response after two months of treatment with the maximum recommended dose of 145 mg per day.

Pancreatitis

Pancreatitis has been reported in patients taking fenofibrate, gemfibrozil, and clofibrate. This occurrence may represent a failure of efficacy in patients with severe hypertriglyceridemia, a direct drug effect, or a secondary phenomenon mediated through biliary tract stone or sludge formation with obstruction of the common bile duct.

Hypersensitivity Reactions

Acute hypersensitivity reactions including severe skin rashes requiring patient hospitalization and treatment with steroids have occurred very rarely during treatment with fenofibrate, including rare spontaneous reports of Stevens-Johnson syndrome, and toxic epidermal necrolysis. Urticaria was seen in 1.1 vs. 0%, and rash in 1.4 vs. 0.8% of fenofibrate and placebo patients respectively in controlled trials.

Hematologic Changes

Mild to moderate hemoglobin, hematocrit, and white blood cell decreases have been observed in patients following initiation of fenofibrate therapy. However, these levels stabilize during long-term administration. Extremely rare spontaneous reports of thrombocytopenia and agranulocytosis have been received during post-marketing surveillance outside of the U.S. Periodic blood counts are recommended during the first 12 months of TRICOR administration.

Skeletal Muscle

The use of fibrates alone, including TRICOR, may occasionally be associated with myopathy. Treatment with drugs of the fibrate class has been associated on rare occasions with rhabdomyolysis, usually in patients with impaired renal function. Myopathy should be considered in any patient with diffuse myalgias, muscle tenderness or weakness, and/or marked elevations of creatine phosphokinase levels.

Patients should be advised to report promptly unexplained muscle pain, tenderness or weakness, particularly if accompanied by malaise or fever. CPK levels should be assessed in patients reporting these symptoms, and fenofibrate therapy should be discontinued if markedly elevated CPK levels occur or myopathy is diagnosed.

Venothromboembolic Disease

In the FIELD trial, pulmonary embolus (PE) and deep vein thrombosis (DVT) were observed at higher rates in the fenofibrate- than the placebo-treated group. Of 9,795 patients enrolled in FIELD, there were 4,900 in the placebo group and 4,895 in the fenofibrate group. For DVT, there were 48 events (1%) in the placebo group and 67 (1%) in the fenofibrate group (p = 0.074); and for PE, there were 32 (0.7%) events in the placebo group and 53 (1%) in the fenofibrate group (p = 0.022).

In the Coronary Drug Project, a higher proportion of the clofibrate group experienced definite or suspected fatal or nonfatal pulmonary embolism or thrombophlebitis than the placebo group (5.2% vs. 3.3% at five years; p < 0.01).

Serum Creatinine

Elevations in serum creatinine have been reported in patients on fenofibrate. These elevations tend to return to baseline following discontinuation of fenofibrate. The clinical significance of these observations is unknown.

Drug Interactions

Oral Anticoagulants

CAUTION SHOULD BE EXERCISED WHEN COUMARIN ANTICOAGULANTS ARE GIVEN IN CONJUNCTION WITH TRICOR. THE DOSAGE OF THE ANTICOAGULANTS SHOULD BE REDUCED TO MAINTAIN THE PROTHROMBIN TIME/INR AT THE DESIRED LEVEL TO PREVENT BLEEDING COMPLICATIONS. FREQUENT PROTHROMBIN TIME/INR DETERMINATIONS ARE ADVISABLE UNTIL IT HAS BEEN DEFINITELY DETERMINED THAT THE PROTHROMBIN TIME/INR HAS STABILIZED.

HMG-CoA Reductase Inhibitors

The combined use of TRICOR and HMG-CoA reductase inhibitors should be avoided unless the benefit of further alterations in lipid levels is likely to outweigh the increased risk of this drug combination (see WARNINGS).

Resins

Since bile acid sequestrants may bind other drugs given concurrently, patients should take TRICOR at least 1 hour before or 4-6 hours after a bile acid binding resin to avoid impeding its absorption.

Cyclosporine

Because cyclosporine can produce nephrotoxicity with decreases in creatinine clearance and rises in serum creatinine, and because renal excretion is the primary elimination route of fibrate drugs including TRICOR, there is a risk that an interaction will lead to deterioration. The benefits and risks of using TRICOR (fenofibrate tablets) with immunosuppressants and other potentially nephrotoxic agents should be carefully considered, and the lowest effective dose employed.

Carcinogenesis, Mutagenesis, Impairment of Fertility

Two dietary carcinogenicity studies have been conducted in rats with fenofibrate. In the first 24-month study, rats were dosed with fenofibrate at 10, 45, and 200 mg/kg/day, approximately 0.3, 1, and 6 times the maximum recommended human dose (MRHD), based on body surface area comparisons (mg/m^2). At a dose of 200 mg/kg/day (at 6 times the MRHD), the incidence of liver carcinomas was significantly increased in both sexes. A statistically significant increase in pancreatic carcinomas was observed in males at 1 and 6 times the MRHD; an increase in pancreatic adenomas and benign testicular interstitial cell tumors was observed at 6 times the MRHD in males. In a second 24-month rat carcinogenicity study in a different strain of rats, doses of 10 and 60 mg/kg/day (0.3 and 2 times the MRHD) produced significant increases in the incidence of pancreatic acinar adenomas in both sexes and increases in testicular interstitial cell tumors in males at 2 times the MRHD.

A 117-week carcinogenicity study was conducted in rats comparing three drugs: fenofibrate 10 and 60 mg/kg/day (0.3 and 2 times the MRHD), clofibrate (400 mg/kg/day; 2 times the human dose), and gemfibrozil (250 mg/kg/day; 2 times the human dose, based on mg/m^2 surface area). Fenofibrate increased pancreatic acinar adenomas in both sexes. Clofibrate increased hepatocellular carcinoma and pancreatic acinar adenomas in males and hepatic neoplastic nodules in females. Gemfibrozil increased hepatic neoplastic nodules in males and females, while all three drugs increased testicular interstitial cell tumors in males.

In a 21-month study in mice, fenofibrate 10, 45, and 200 mg/kg/day (approximately 0.2, 1, and 3 times the MRHD on the basis of mg/m^2 surface area) significantly increased the liver carcinomas in both sexes at 3 times the MRHD. In a second 18-month study at 10, 60, and 200 mg/kg/day, fenofibrate significantly increased the liver carcinomas in male mice and liver adenomas in female mice at 3 times the MRHD.

Electron microscopy studies have demonstrated peroxisomal proliferation following fenofibrate administration to the rat. An adequate study to test for peroxisome proliferation in humans has not been done, but changes in peroxisome morphology and numbers have been observed in humans after treatment with other members of the fibrate class when liver biopsies were compared before and after treatment in the same individual.

Fenofibrate has been demonstrated to be devoid of mutagenic potential in the following tests: Ames, mouse lymphoma, chromosomal aberration and unscheduled DNA synthesis in primary rat hepatocytes.

In fertility studies rats were given oral dietary doses of fenofibrate, males received 61 days prior to mating and females 15 days prior to mating through weaning which resulted in no adverse effect on fertility at doses up to 300 mg/kg/day (~10 times the MRHD, based on mg/m^2 surface area comparisons).

Pregnancy

Pregnancy Category C

Safety in pregnant women has not been established. There are no adequate and well controlled studies of fenofibrate in pregnant women. Fenofibrate should be used during pregnancy only if the potential benefit justifies the potential risk to the fetus.

In female rats given oral dietary doses of 15, 75, and 300 mg/kg/day of fenofibrate from 15 days prior to mating through weaning, maternal toxicity was observed at 0.3 times the MRHD, based on body surface area comparisons; mg/m^2.

In pregnant rats given oral dietary doses of 14, 127, and 361 mg/kg/day from gestation day 6-15 during the period of organogenesis, adverse developmental findings were not observed at 14 mg/kg/day (less than 1 times the MRHD, based on body surface area comparisons; mg/m^2). At higher multiples of human doses evidence of maternal toxicity was observed.

In pregnant rabbits given oral gavage doses of 15, 150, and 300 mg/kg/day from gestation day 6-18 during the period of organogenesis and allowed to deliver, aborted litters were observed at 150 mg/kg/day (10 times the MRHD, based on body surface area comparisons: mg/m^2). No developmental findings were observed at 15 mg/kg/day (at less than 1 times the MRHD, based on body surface area comparisons; mg/m^2).

In pregnant rats given oral dietary doses of 15, 75, and 300 mg/kg/day from gestation day 15 through lactation day 21 (weaning), maternal toxicity was observed at less than 1 times the MRHD, based on body surface area comparisons; mg/m^2.

Nursing Mothers

It is not known whether fenofibrate is excreted into milk. Because many drugs are excreted in human milk and because of the potential for serious adverse reactions in nursing infants from fenofibrate, a decision should be made whether to discontinue nursing or administration of fenofibrate taking into account the importance of the drug to the lactating woman.

Pediatric Use

Safety and efficacy in pediatric patients have not been established.

Geriatric Use

Fenofibric acid is known to be substantially excreted by the kidney, and the risk of adverse reactions to this drug may be greater in patients with impaired renal function. Fenofibric acid exposure is not influenced by age. However, elderly patients have a higher incidence of renal impairment, such that dose selection for the elderly should be made on the basis of renal function (see CLINICAL PHARMACOLOGY, Special Populations, Renal Insufficiency). Elderly patients with normal renal function should require no dose modifications.

ADVERSE REACTIONS

Adverse events reported by 2% or more of patients treated with fenofibrate during the double-blind, placebo-controlled trials, regardless of causality, are listed in the table below. Adverse events led to discontinuation of treatment in 5.0% of patients treated with fenofibrate and in 3.0% treated with placebo. Increases in liver function tests were the most frequent events, causing discontinuation of fenofibrate treatment in 1.6% of patients in double-blind trials.

BODY SYSTEM | Fenofibrate* | Placebo
Adverse Event | (N=439) | (N=365)
BODY AS A WHOLE
Abdominal Pain | 4.6% | 4.4%
Back Pain | 3.4% | 2.5%
Headache | 3.2% | 2.7%
Asthenia | 2.1% | 3.0%
Flu Syndrome | 2.1% | 2.7%
DIGESTIVE
Liver Function Tests Abnormal | 7.5%** | 1.4%
Diarrhea | 2.3% | 4.1%
Nausea | 2.3% | 1.9%
Constipation | 2.1% | 1.4%
METABOLIC AND NUTRITIONAL DISORDERS
SGPT Increased | 3.0% | 1.6%
Creatine Phosphokinase Increased | 3.0% | 1.4%
SGOT Increased | 3.4% ** | 0.5%
RESPIRATORY
Respiratory Disorder | 6.2% | 5.5%
Rhinitis | 2.3% | 1.1%
* Dosage equivalent to 145 mg TRICOR.
** Significantly different from Placebo.

Additional adverse events reported during post-marketing surveillance or by three or more patients in placebo-controlled trials or reported in other controlled or open trials, regardless of causality are listed below.

Body as a Whole

Accidental injury, allergic reaction, chest pain, cyst, fever, hernia, infection, malaise and pain (unspecified).

Cardiovascular System

Angina pectoris, arrhythmia, atrial fibrillation, cardiovascular disorder, coronary artery disorder, electrocardiogram abnormal, extrasystoles, hypertension, hypotension, migraine, myocardial infarct, palpitation, peripheral vascular disorder, phlebitis, tachycardia, varicose vein, vascular disorder, vasodilatation, venous thromboembolic events (deep vein thrombosis, pulmonary embolus) and ventricular extrasystoles.

Digestive System

Anorexia, cholecystitis, cholelithiasis, colitis, diarrhea, duodenal ulcer, dyspepsia, eructation, esophagitis, flatulence, gastritis, gastroenteritis, gastrointestinal disorder, increased appetite, jaundice, liver fatty deposit, nausea, pancreatitis, peptic ulcer, rectal disorder, rectal hemorrhage, tooth disorder and vomiting.

Endocrine System

Diabetes mellitus.

Hemic and Lymphatic System

Anemia, ecchymosis, eosinophilia, leukopenia, lymphadenopathy, and thrombocytopenia.

Laboratory Investigations

Alkaline phosphatase increased, bilirubin increased, blood urea nitrogen increased, serum creatinine increased, gamma glutamyl transpeptidase increased, lactate dehydrogenase increased, SGOT and SGPT increased.

Metabolic and Nutritional Disorders

Edema, gout, hyperuricemia, hypoglycemia, peripheral edema, weight gain, and weight loss.

Musculoskeletal System

Arthralgia, arthritis, arthrosis, bursitis, joint disorder, leg cramps, myalgia, myasthenia, myositis, rhabdomyolysis and tenosynovitis.

Nervous System

Anxiety or nervousness, depression, dizziness, dry mouth, hypertonia, insomnia, libido decreased, neuralgia, paresthesia, somnolence and vertigo.

Respiratory System

Allergic pulmonary alveolitis, asthma, bronchitis, cough increased, dyspnea, laryngitis, pharyngitis, pneumonia and sinusitis.

Skin and Appendages

Acne, alopecia, contact dermatitis, eczema, fungal dermatitis, herpes simplex, herpes zoster, maculopapular rash, nail disorder, photosensitivity reaction, pruritus, rash, sweating, skin disorder, skin ulcer and urticaria.

Special Senses

Abnormal vision, amblyopia, cataract specified, conjunctivitis, ear pain, eye disorder, otitis media and refraction disorder.

Urogenital System

Abnormal kidney function, cystitis, dysuria, gynecomastia, prostatic disorder, unintended pregnancy, urinary frequency, urolithiasis and vaginal moniliasis.

OVERDOSAGE

There is no specific treatment for overdose with TRICOR. General supportive care of the patient is indicated, including monitoring of vital signs and observation of clinical status, should an overdose occur. If indicated, elimination of unabsorbed drug should be achieved by emesis or gastric lavage; usual precautions should be observed to maintain the airway. Because fenofibrate is highly bound to plasma proteins, hemodialysis should not be considered.

DOSAGE AND ADMINISTRATION

Patients should be placed on an appropriate lipid-lowering diet before receiving TRICOR, and should continue this diet during treatment with TRICOR. TRICOR tablets can be given without regard to meals.

For the treatment of adult patients with primary hypercholesterolemia or mixed hyperlipidemia, the initial dose of TRICOR is 145 mg per day.

For adult patients with hypertriglyceridemia, the initial dose is 48 to 145 mg per day. Dosage should be individualized according to patient response, and should be adjusted if necessary following repeat lipid determinations at 4 to 8 week intervals. The maximum dose is 145 mg per day.

Treatment with TRICOR should be initiated at a dose of 48 mg/day in patients having mild to moderately impaired renal function, and increased only after evaluation of the effects on renal function and lipid levels at this dose.

Lipid levels should be monitored periodically and consideration should be given to reducing the dosage of TRICOR if lipid levels fall significantly below the targeted range.

HOW SUPPLIED

TRICOR® (fenofibrate tablets) is available in two strengths:

48 mg yellow tablets, imprinted with “Abbott “A” logo” and Abbo-Code identification letters "FI", available in:

bottles of 30 (NDC 54868-5224-0),

bottles of 90 (NDC 54868-5224-1).

145 mg white tablets, imprinted with “Abbott “A” logo”and Abbo-Code identification letters "FO", available in:

bottles of 30 (NDC 54868-5203-0),

bottles of 90 (NDC 54868-5203-1).

Storage

Store at 25°C (77°F); excursions permitted to 15-30°C (59-86°F).

[See USP Controlled Room Temperature]. Keep out of the reach of children. Protect from moisture.

Manufactured for Abbott Laboratories, North Chicago, IL 60064, U.S.A.

by Fournier Laboratories Ireland Limited, Anngrove, Carrigtwohill Co. Cork, Ireland.

Relabeling and Repackaging by:
Physicians Total Care, Inc.
Tulsa, OK 74146

REFERENCES

1. GOLDBERG AC, et al. Fenofibrate for the Treatment of Type IV and V Hyperlipoproteinemias: A Double-Blind, Placebo-Controlled Multicenter US Study. Clinical Therapeutics, 11, pp. 69-83, 1989.
2. NIKKILA EA. Familial Lipoprotein Lipase Deficiency and Related Disorders of Chylomicron Metabolism. In Stanbury J.B., et al. (eds.): The Metabolic Basis of Inherited Disease, 5th edition, McGraw-Hill, 1983, Chap. 30, pp. 622-642.
3. BROWN WV, et al. Effects of Fenofibrate on Plasma Lipids: Double-Blind, Multicenter Study In Patients with Type IIA or IIB Hyperlipidemia. Arteriosclerosis . 6, pp. 670-678, 1986.

Abbott Laboratories North Chicago, IL 60064, U.S.A.

Rev. 12/2008

PACKAGE LABEL

TriCor® Fenofibrate Tablets

48 mg

PACKAGE LABEL

TriCor® Fenofibrate Tablets
145 mg